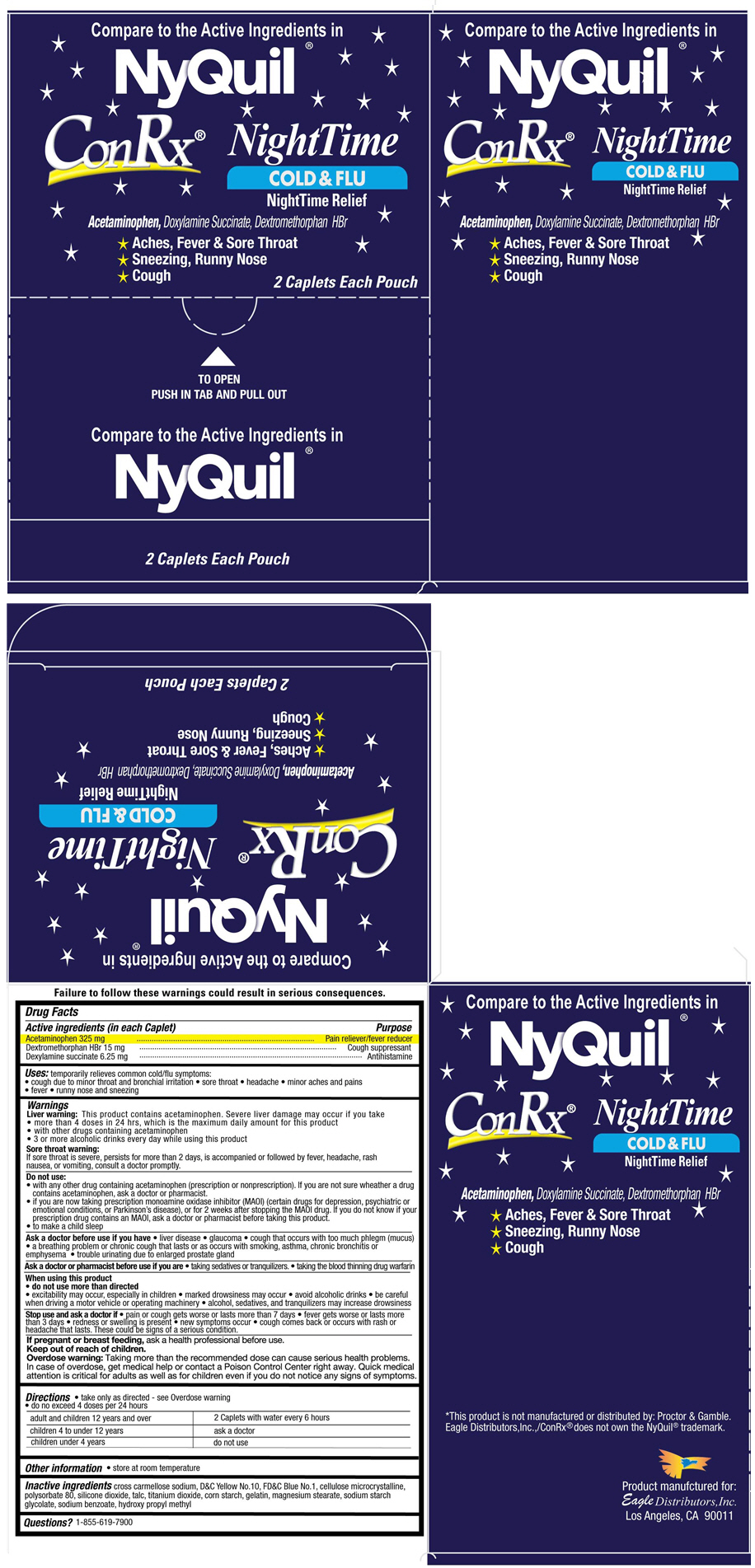 DRUG LABEL: ConRx NightTime
NDC: 68737-239 | Form: TABLET
Manufacturer: Eagle Distributors,Inc.
Category: otc | Type: HUMAN OTC DRUG LABEL
Date: 20140211

ACTIVE INGREDIENTS: Acetaminophen 325 mg/1 1; Dextromethorphan Hydrobromide 15 mg/1 1; Doxylamine Succinate 6.25 mg/1 1
INACTIVE INGREDIENTS: CROSCARMELLOSE SODIUM; FD&C BLUE NO. 1; D&C YELLOW NO. 10; CELLULOSE, MICROCRYSTALLINE; POLYSORBATE 80; SILICON DIOXIDE; TALC; TITANIUM DIOXIDE; STARCH, CORN; GELATIN; MAGNESIUM STEARATE; SODIUM STARCH GLYCOLATE TYPE A POTATO; SODIUM BENZOATE; HYPROMELLOSES; ETHYLCELLULOSES

ConRx® NightTime

Drug Facts

ACTIVE INGREDIENT

Active ingredients (in each Caplet) | Purpose
Acetaminophen 325 mg | Pain reliever/fever reducer
Dextromethorphan HBr 15 mg | Cough suppressant
Dexylamine succinate 6.25 mg | Antihistamine

Uses

temporarily relieves common cold/flu symptoms:

- cough due to minor throat and bronchial irritation
- sore throat
- headache
- minor aches and pains
- fever
- runny nose and sneezing

Warnings

Liver warning

This product contains acetaminophen. Severe liver damage may occur if you take

- more than 4 doses in 24 hrs, which is the maximum daily amount for this product
- with other drugs containing acetaminophen
- 3 or more alcoholic drinks every day while using this product

Sore throat warning

If sore throat is severe, persists for more than 2 days, is accompanied or followed by fever, headache, rash nausea, or vomiting, consult a doctor promptly.

Do not use

- with any other drug containing acetaminophen (prescription or nonprescription). If you are not sure wheather a drug contains acetaminophen, ask a doctor or pharmacist.
- if you are now taking prescription monoamine oxidase inhibitor (MAOI) (certain drugs for depression, psychiatric or emotional conditions, or Parkinson's disease), or for 2 weeks after stopping the MAOI drug. If you do not know if your prescription drug contains an MAOI, ask a doctor or pharmacist before taking this product.
- to make a child sleep

Ask a doctor before use if you have

- liver disease
- glaucoma
- cough that occurs with too much phlegm (mucus)
- a breathing problem or chronic cough that lasts or as occurs with smoking, asthma, chronic bronchitis or emphysema
- trouble urinating due to enlarged prostate gland

Ask a doctor or pharmacist before use if you are

- taking sedatives or tranquilizers.
- taking the blood thinning drug warfarin

When using this product

- do not use more than directed
- excitability may occur, especially in children
- marked drowsiness may occur
- avoid alcoholic drinks
- be careful when driving a motor vehicle or operating machinery
- alcohol, sedatives, and tranquilizers may increase drowsiness

Stop use and ask a doctor if

- pain or cough gets worse or lasts more than 7 days
- fever gets worse or lasts more than 3 days
- redness or swelling is present
- new symptoms occur
- cough comes back or occurs with rash or headache that lasts. These could be signs of a serious condition.

PREGNANCY OR BREAST FEEDING

If pregnant or breast-feeding, ask a health professional before use.

Keep out of reach of children.

Overdose warning

Taking more than directed can cause serious health problems. In case of overdose, get medical help or contact a Poison Control Center right away. Quick medical attention is critical for adults & for children even if you do not notice any signs or symptoms.

Directions

- take only as directed - see Overdose warning
- do no exceed 4 doses per 24 hours

adult and children 12 years and over, 2 Caplets with water every 6 hours
children 4 to under 12 years, ask a doctor
children under 4 years, do not use

Other information

- store at room temperature

Inactive ingredients

cross carmellose sodium, D&C Yellow No.10, FD&C Blue No.1, cellulose microcrystalline, polysorbate 80, silicone dioxide, talc, titanium dioxide, corn starch, gelatin, magnesium stearate, sodium starch glycolate, sodium benzoate, hydroxy propyl methyl

Questions?

1-855-619-7900

PRINCIPAL DISPLAY PANEL - 50 x 2 Caplet Pouch Box

Compare to the Active Ingredients in
NyQuil®

ConRx® NightTime
COLD & FLU
NightTime Relief

Acetaminophen, Doxylamine Succinate, Dextromethorphan HBr

⋆ Aches, Fever & Sore Throat
⋆ Sneezing, Runny Nose
⋆ Cough

2 Caplets Each Pouch

TO OPEN
PUSH IN TAB AND PULL OUT

Compare to the Active Ingredients in
NyQuil®

2 Caplets Each Pouch